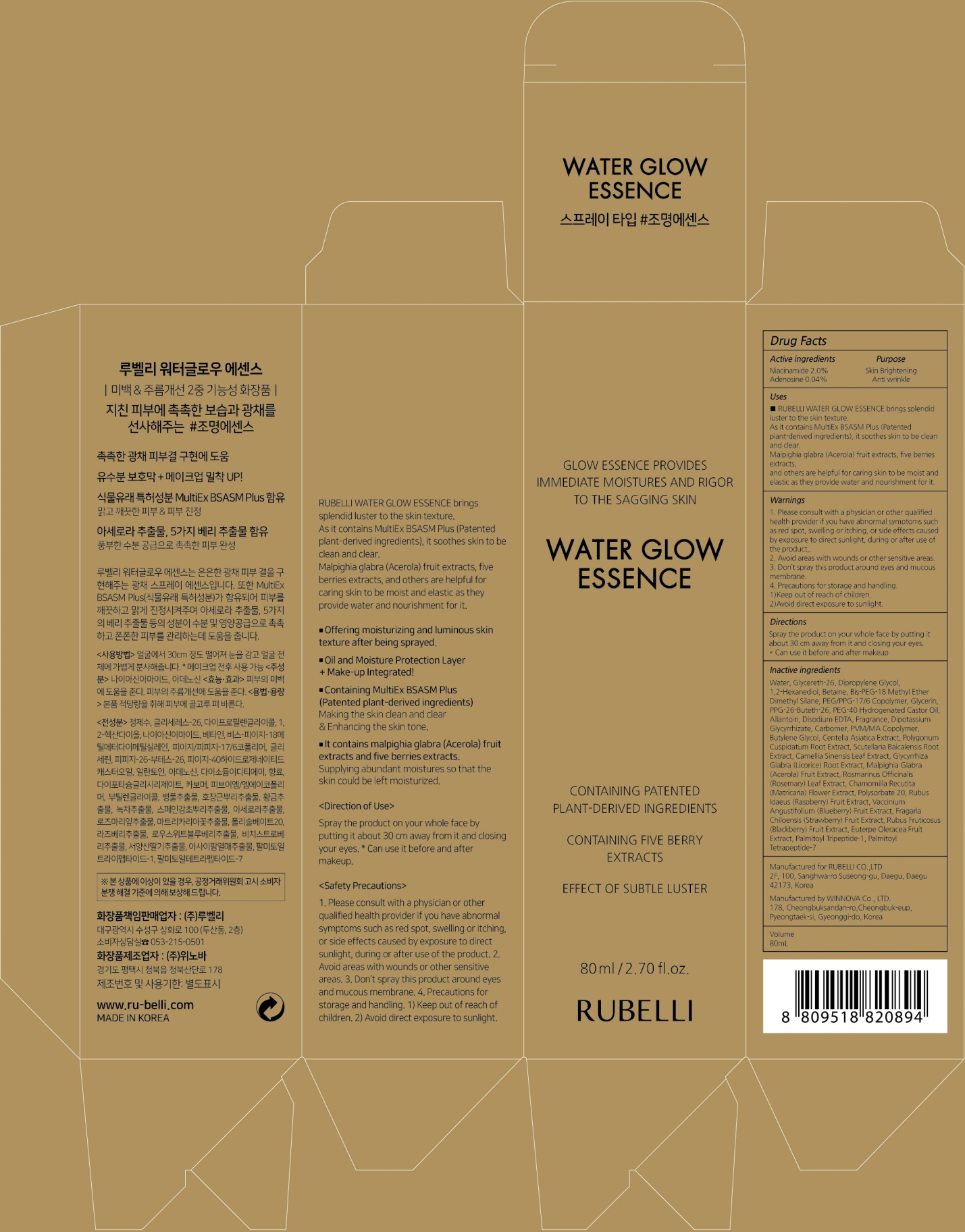 DRUG LABEL: RUBELLI WATER GLOW ESSENCE
NDC: 71006-070 | Form: SPRAY
Manufacturer: RUBELLI CO.,LTD
Category: otc | Type: HUMAN OTC DRUG LABEL
Date: 20190418

ACTIVE INGREDIENTS: Niacinamide 1.60 g/80 mL; Adenosine 0.03 g/80 mL
INACTIVE INGREDIENTS: Water; Dipropylene Glycol

ACTIVE INGREDIENT

Active Ingredient: Niacinamide 2.0%, Adenosine 0.04%

INACTIVE INGREDIENT

Inactive Ingredients:

Water, Glycereth-26, Dipropylene Glycol, 1,2-Hexanediol, Niacinamide, Betaine, Bis-PEG-18 Methyl Ether Dimethyl Silane, PEG/PPG-17/6 Copolymer, Glycerin, PPG-26-Buteth-26, PEG-40 Hydrogenated Castor Oil, Allantoin, Adenosine, Disodium EDTA, Fragrance, Dipotassium Glycyrrhizate, Carbomer, PVM/MA Copolymer, Butylene Glycol, Centella Asiatica Extract, Polygonum Cuspidatum Root Extract, Scutellaria Baicalensis Root Extract, Camellia Sinensis Leaf Extract, Glycyrrhiza Glabra (Licorice) Root Extract, Malpighia Glabra (Acerola) Fruit Extract, Rosmarinus Officinalis (Rosemary) Leaf Extract, Chamomilla Recutita (Matricaria) Flower Extract, Polysorbate 20, Rubus Idaeus (Raspberry) Fruit Extract, Vaccinium Angustifolium (Blueberry) Fruit Extract, Fragaria Chiloensis (Strawberry) Fruit Extract, Rubus Fruticosus (Blackberry) Fruit Extract, Euterpe Oleracea Fruit Extract, Palmitoyl Tripeptide-1, Palmitoyl Tetrapeptide-7

PURPOSE

Purpose: Skin Brightening & anti wrinkle

WARNINGS

1. Please consult with a physician or other qualified health provider if you have abnormal symptoms such as red spot, swelling or itching, or side effects caused by exposure to direct sunlight, during or after use of the product. 2. Avoid areas with wounds or other sensitive areas. 3. Don’t spray this product around eyes and mucous membrane! 4. Precautions for storage and handling. 1)Keep out of reach of children. 2)Avoid direct exposure to sunlight.

KEEP OUT OF REACH OF CHILDREN

Use

RUBELLI WATER GLOW Essence brings splendid luster to the skin texture.
As it contains MultiEx BSASM Plus (Patented plant-derived ingredients), it soothes skin to be clean and clear.
Malpighia glabra (Acerola) fruit extracts, five berries extracts, and others are helpful for caring skin to be moist and elastic as they provide water and nourishment for it.

Directions

Spray the product on your whole face by putting it about 30 cm away from it and closing your eyes.
* Can use it before and after makeup